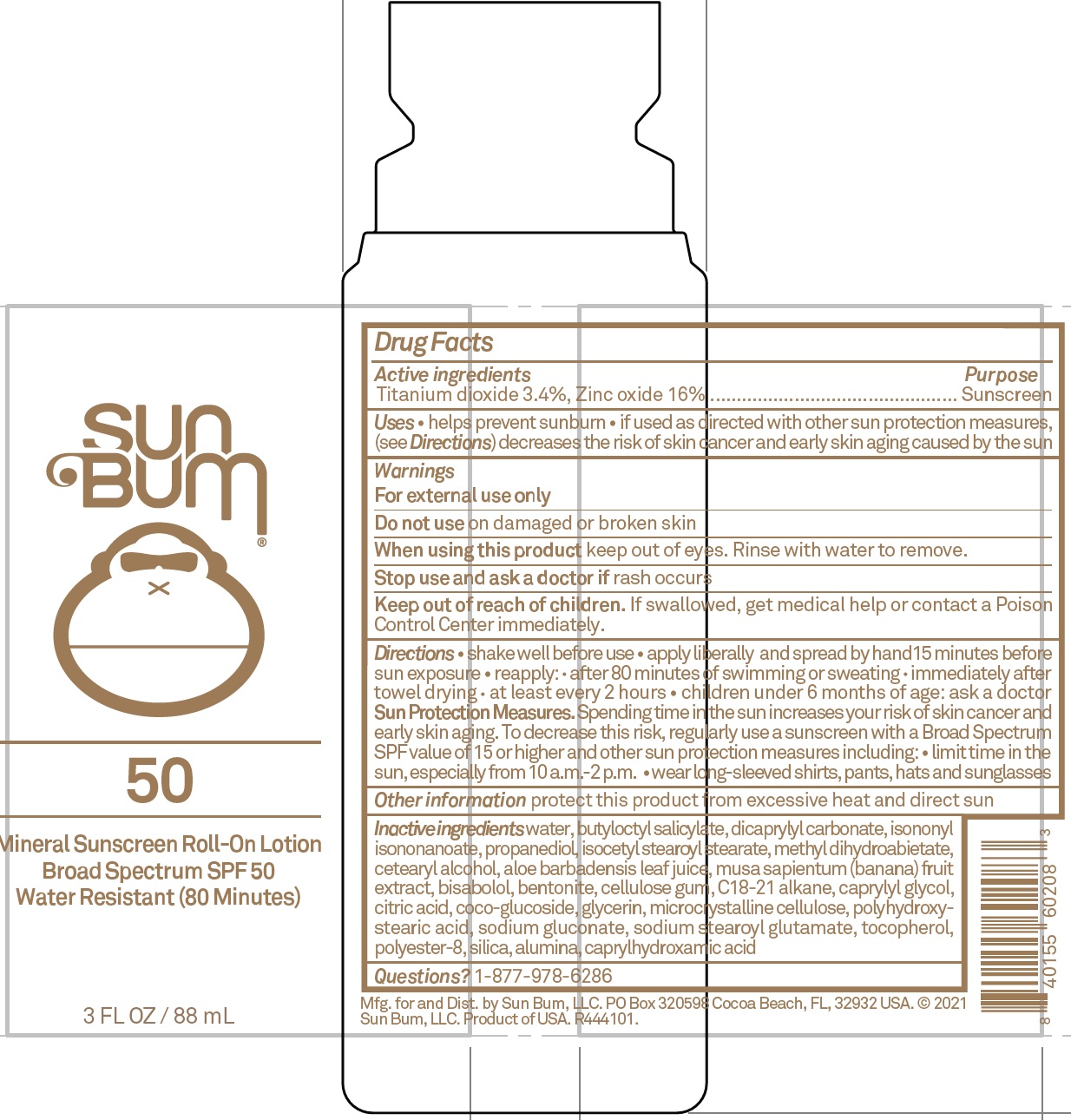 DRUG LABEL: Sun Bum Mineral Sunscreen Roll On SPF 50
NDC: 69039-641 | Form: LOTION
Manufacturer: Sun Bum LLC
Category: otc | Type: HUMAN OTC DRUG LABEL
Date: 20220204

ACTIVE INGREDIENTS: TITANIUM DIOXIDE 34 mg/1 mL; ZINC OXIDE 160 mg/1 mL
INACTIVE INGREDIENTS: WATER; BUTYLOCTYL SALICYLATE; DICAPRYLYL CARBONATE; ISONONYL ISONONANOATE; PROPANEDIOL; ISOCETYL STEAROYL STEARATE; METHYL DIHYDROABIETATE; CETOSTEARYL ALCOHOL; ALOE VERA LEAF; BANANA; LEVOMENOL; BENTONITE; CARBOXYMETHYLCELLULOSE SODIUM, UNSPECIFIED; C18-C21 ALKANE; CAPRYLYL GLYCOL; CITRIC ACID MONOHYDRATE; COCO GLUCOSIDE; GLYCERIN; MICROCRYSTALLINE CELLULOSE; SODIUM GLUCONATE; SODIUM STEAROYL GLUTAMATE; TOCOPHEROL; POLYESTER-8 (1400 MW, CYANODIPHENYLPROPENOYL CAPPED); SILICON DIOXIDE; ALUMINUM OXIDE; CAPRYLHYDROXAMIC ACID

Sun Bum Mineral Sunscreen Roll On Lotion SPF 50

Active ingredients

Titanium dioxide 3.4%, Zinc oxide 16%

Purpose

Sunscreen

Uses

• helps prevent sunburn • if used as directed with other sun protection measures, (see Directions) decreases the risk of skin cancer and early skin aging caused by the sun

Warnings

For external use only

Do not use

on damaged or broken skin

When using this product

keep out of eyes. Rinse with water to remove.

Stop use and ask a doctor if

rash occurs

Keep out of reach of children.

If swallowed, get medical help or contact a Poison Control Center immediately.

Directions

• shake well before use • apply liberally and spread by hand15 minutes before sun exposure • reapply: • after 80 minutes of swimming or sweating • immediately after towel drying • at least every 2 hours • children under 6 months of age: ask a doctor
Sun Protection Measures. Spending time in the sun increases your risk of skin cancer and early skin aging. To decrease this risk, regularly use a sunscreen with a Broad Spectrum SPF value of 15 or higher and other sun protection measures including: • limit time in the sun, especially from 10 a.m.-2 p.m. • wear long-sleeved shirts, pants, hats and sunglasses

Other information

protect this product from excessive heat and direct sun

Inactive ingredients

water, butyloctyl salicylate, dicaprylyl carbonate, isononyl isononanoate, propanediol, isocetyl stearoyl stearate, methyl dihydroabietate, cetearyl alcohol, aloe barbadensis leaf juice, musa sapientum (banana) fruit extract, bisabolol, bentonite, cellulose gum, C18-21 alkane, caprylyl glycol, citric acid, coco-glucoside, glycerin, microcrystalline cellulose, polyhydroxystearic acid, sodium gluconate, sodium stearoyl glutamate, tocopherol, polyester-8, silica, alumina, caprylhydroxamic acid

Questions?

1-877-978-6286